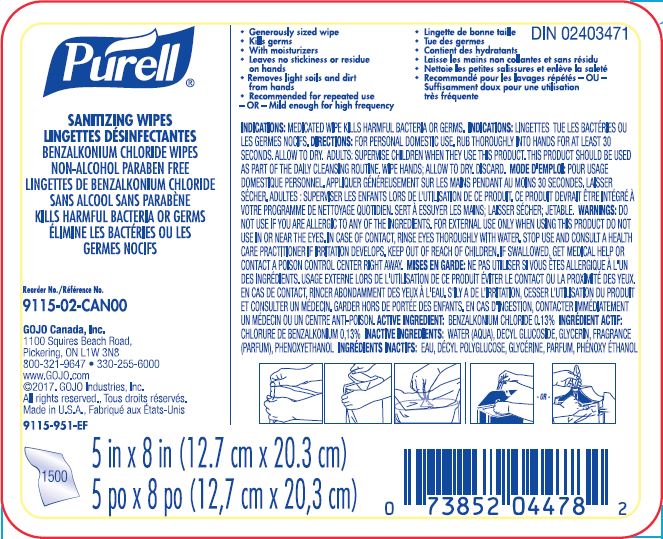 DRUG LABEL: PURELL Sanitizing Wipes
NDC: 21749-303 | Form: CLOTH
Manufacturer: GOJO Industries, Inc.
Category: otc | Type: HUMAN OTC DRUG LABEL
Date: 20250110

ACTIVE INGREDIENTS: BENZALKONIUM CHLORIDE 0.13 mg/100 mL
INACTIVE INGREDIENTS: WATER; DECYL GLUCOSIDE; GLYCERIN; PHENOXYETHANOL

PURELL Sanitizing Wipes